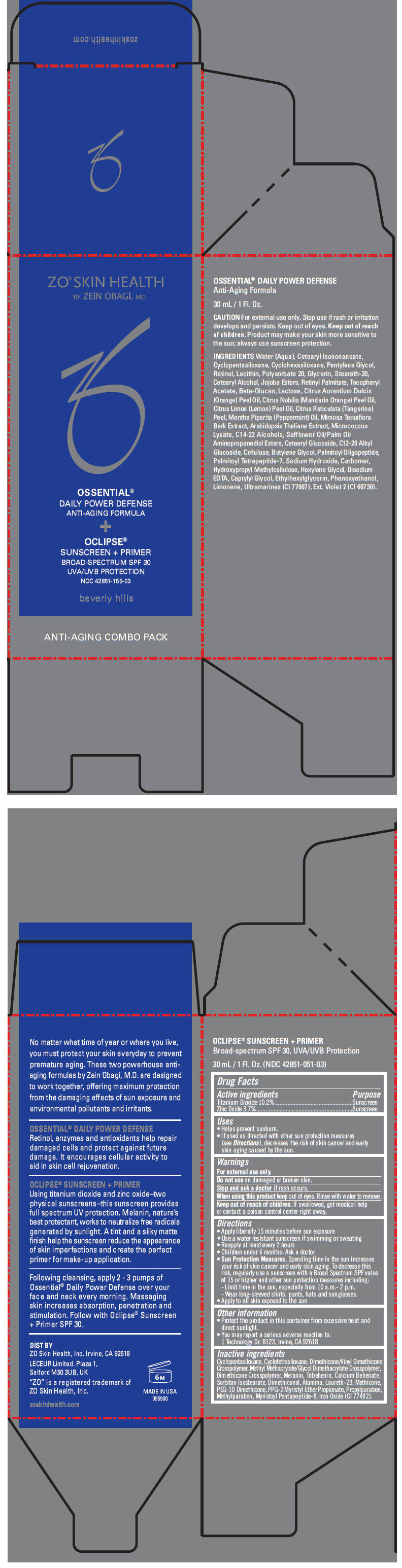 DRUG LABEL: ZO SKIN HEALTH
NDC: 42851-155 | Form: KIT | Route: TOPICAL
Manufacturer: ZO Skin Health, Inc.
Category: otc | Type: HUMAN OTC DRUG LABEL
Date: 20140422

ACTIVE INGREDIENTS: TITANIUM DIOXIDE 102 mg/1 mL; ZINC OXIDE 37 mg/1 mL
INACTIVE INGREDIENTS: CYCLOMETHICONE 5; CYCLOMETHICONE 4; DIMETHICONE/VINYL DIMETHICONE CROSSPOLYMER (SOFT PARTICLE); METHYL METHACRYLATE/GLYCOL DIMETHACRYLATE CROSSPOLYMER; TRIBEHENIN; CALCIUM BEHENATE; SORBITAN ISOSTEARATE; DIMETHICONOL (40 CST); ALUMINUM OXIDE; LAURETH-23; METHICONE (20 CST); PEG-10 DIMETHICONE (600 CST); PPG-2 MYRISTYL ETHER PROPIONATE; PROPYLPARABEN; METHYLPARABEN; FERRIC OXIDE RED

ZO® SKIN HEALTH
OSSENTIAL® DAILY POWER DEFENSE ANTI-AGING FORMULA + OCLIPSE® SUNSCREEN + PRIMER BROAD SPECTRUM SPF 30 UVA/UVB PROTECTION

Drug Facts

ACTIVE INGREDIENT

Active ingredients | Purpose
Titanium Dioxide 10.2% | Sunscreen
Zinc Oxide 3.7% | Sunscreen

Uses

- Helps prevent sunburn.
- If used as directed with other sun protection measures (see Directions), decreases the risk of skin cancer and early skin aging caused by the sun.

Warnings

For external use only.

Do not use on damaged or broken skin.

Stop and ask a doctor if rash occurs.

When using this product keep out of eyes. Rinse with water to remove.

Keep out of reach of children. If swallowed, get medical help or contact a poison control center right away.

Directions

- Apply liberally 15 minutes before sun exposure
- Use a water resistant sunscreen if swimming or sweating
- Reapply at least every 2 hours
- Children under 6 months: Ask a doctor
- Sun Protection Measures. Spending time in the sun increases your risk of skin cancer and early skin aging. To decrease this risk, regularly use a sunscreen with a Broad Spectrum SPF value of 15 or higher and other sun protection measures including:
  - Limit time in the sun, especially from 10 a.m.- 2 p.m.
  - Wear long-sleeved shirts, pants, hats and sunglasses.
- Apply to all skin exposed to the sun

Other information

- Protect the product in this container from excessive heat and direct sunlight.
- You may report a serious adverse reaction to: 1 Technology Dr. B123, Irvine, CA 92618

Inactive ingredients

Cyclopentasiloxane, Cyclotetrasiloxane, Dimethicone/Vinyl Dimethicone Crosspolymer, Methyl Methacrylate/Glycol Dimethacrylate Crosspolymer, Dimethicone Crosspolymer, Melanin, Tribehenin, Calcium Behenate, Sorbitan Isostearate, Dimethiconol, Alumina, Laureth-23, Methicone, PEG-10 Dimethicone, PPG-2 Myristyl Ether Propionate, Propylparaben, Methylparaben, Myristoyl Pentapeptide-8, Iron Oxide (CI 77492).

DIST BY
ZO Skin Health, Inc. Irvine, CA 92618

PRINCIPAL DISPLAY PANEL - Kit Carton

ZO® SKIN HEALTH
BY ZEIN OBAGI, MD

OSSENTIAL®
DAILY POWER DEFENSE
ANTI-AGING FORMULA
+
OCLIPSE®
SUNSCREEN + PRIMER
BROAD-SPECTRUM SPF 30
UVA/UVB PROTECTION

NDC 42851-155-03

beverly hills

ANTI-AGING COMBO PACK